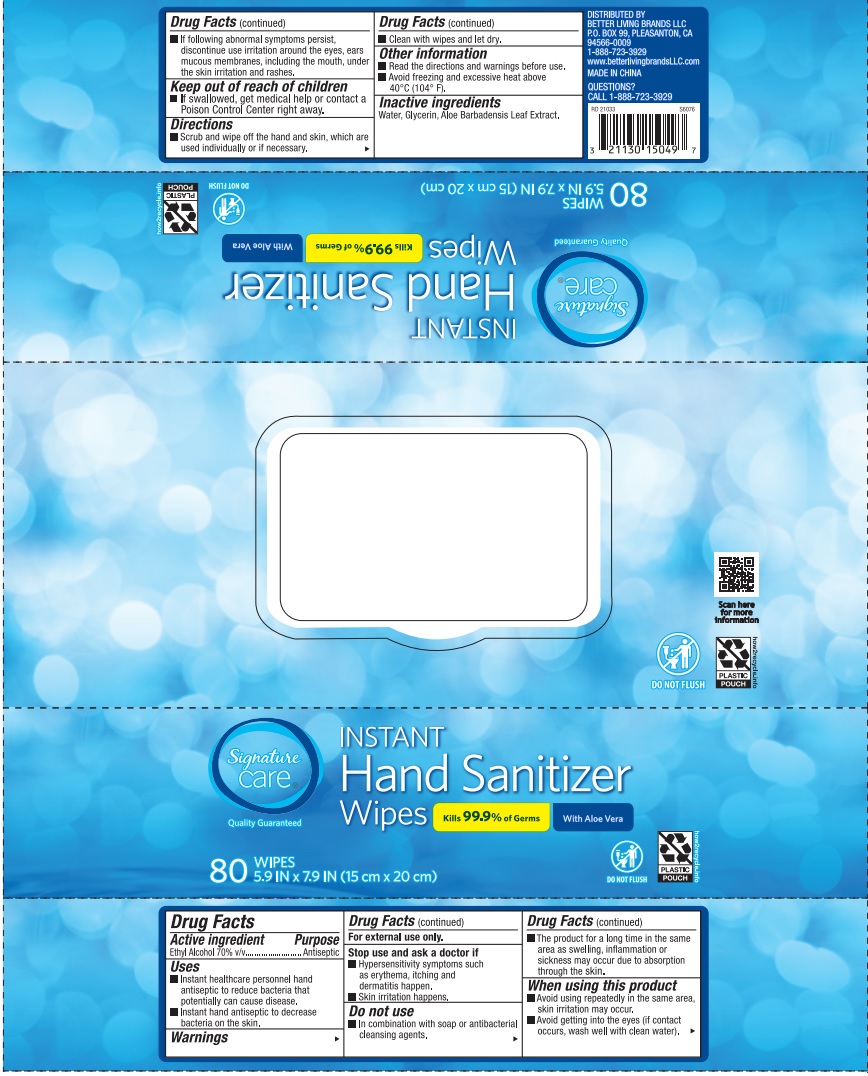 DRUG LABEL: Instant Hand Sanitizizer Wipes
NDC: 75262-201 | Form: SWAB
Manufacturer: ZheJiang Eshine Cosmetic Co Ltd
Category: otc | Type: HUMAN OTC DRUG LABEL
Date: 20250112

ACTIVE INGREDIENTS: ALCOHOL 70 g/100 g
INACTIVE INGREDIENTS: WATER; AMINOMETHYLPROPANOL; GLYCERIN; PROPYLENE GLYCOL; .ALPHA.-TOCOPHEROL ACETATE, D-

Ethyl Alcohol Wipes

Active Ingredient

Ethyl Alcohol 70% v/v

Purpose

Antiseptic

USE

- Instant healthcare personnel hand antiseptic to reduce bacteria that potentially can cause disease.
- Instant hand antiseptic to decrease bacteria on the skin.

Warning

- For external use only.

Stop use and ask a doctor if

- Hypersensitivity symptoms suchas erythema, itching and dermatitis happen.
- Skin irritation happens.
- If dollowing avnomal symptoms persist, discontinue use irritation around the eyes, ears mucous membranes, including the mouth, under the skin irritation and rashes.

Other Information:

- Read the directions and warning before use
- Avoid freezing and excessive heat above 40℃ （104℉）.

KEEP OUT OF REACH OF CHILDREN

●If swallowed, get medical help or contact a Poison Contrl Center right away.

Directions

- Clean with wipes and let dry.

Inactive ingredients

Water, Glycerin, Aloe Barbadensis Leaf Extract